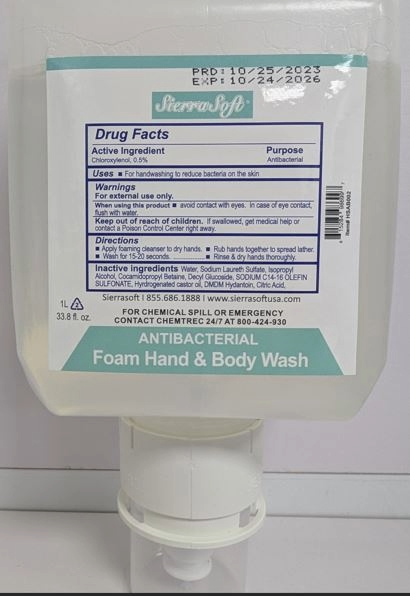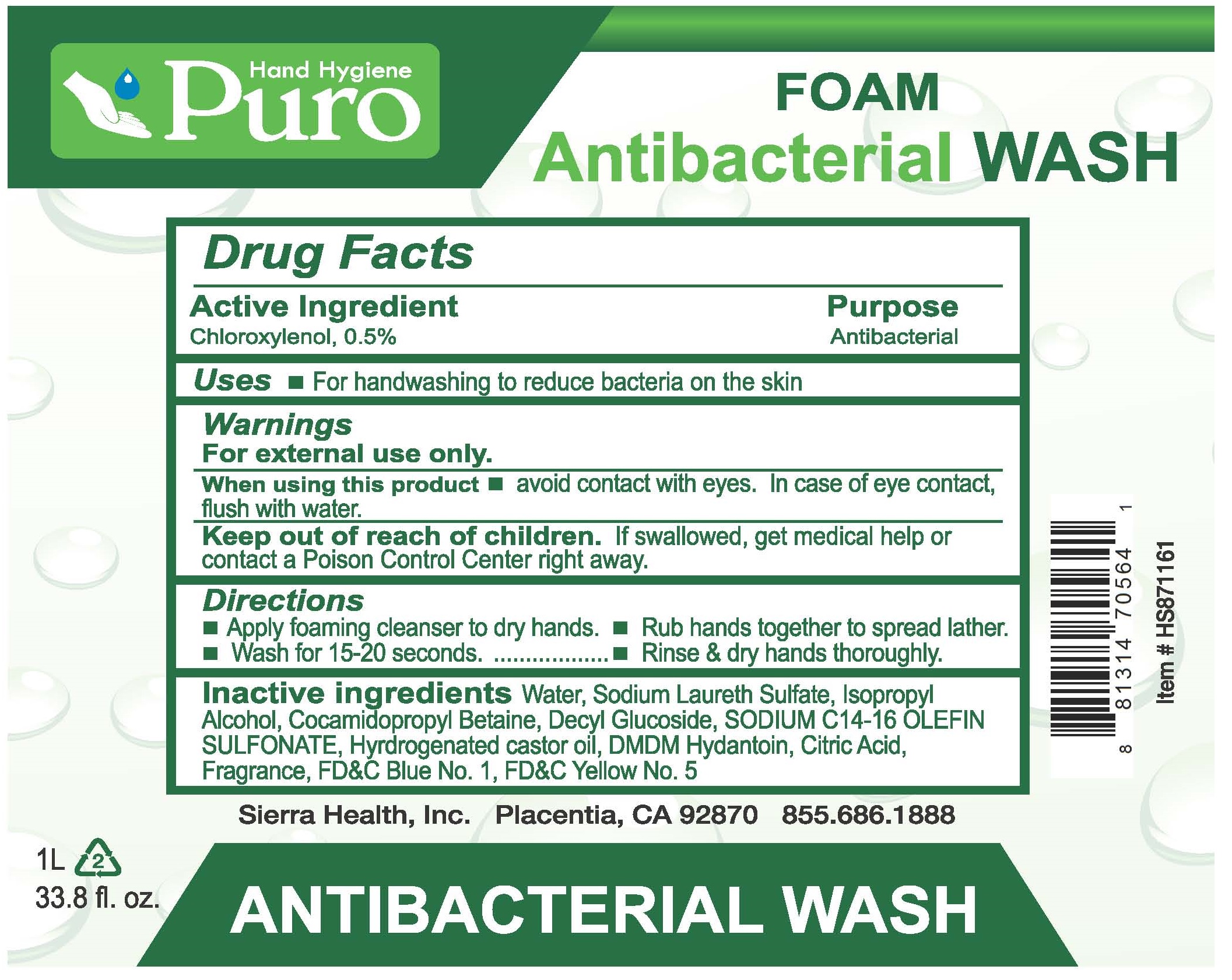 DRUG LABEL: Sierrasoft Clear Antibacterial Wash Foam
NDC: 70415-901 | Form: SOLUTION
Manufacturer: CWGC LA Inc.
Category: otc | Type: HUMAN OTC DRUG LABEL
Date: 20250120

ACTIVE INGREDIENTS: CHLOROXYLENOL 0.5 g/100 mL
INACTIVE INGREDIENTS: WATER; SODIUM LAURETH SULFATE; ISOPROPYL ALCOHOL; COCAMIDOPROPYL BETAINE; DECYL GLUCOSIDE; SODIUM C14-16 OLEFIN SULFONATE; HYDROGENATED CASTOR OIL; DMDM HYDANTOIN; CITRIC ACID MONOHYDRATE

CWGC (as PLD) - Sierrasoft Clear Antibacterial Wash Foam (70415-901)

Active ingredient

Chloroxylenol, 0.5%

Purpose

Antibacterial

Uses

- For handwashing to reduce bacteria on the skin

Warnings

For external use only

When using this product

- Avoid contact with eyes. In case of eye contact, flush with water

Keep out of reach of children. If swallowed, get medical help or contact a Poison Control Center rihgt away.

Directions

- Apply foaming cleanser to dry hands
- Rub hands together to spread lather
- Wash for 15-20 seconds
- Rinse & dry hands thoroughly

Inactive ingredients

Water, Sodium Laureth Sulfate, Isopropyl Alcohol, Cocamidopropyl Betaine, Decyl Glucoside, SODIUM C14-16 OLEFIN SULFONATE, Hydrogenated castor Oil, DMDM Hydantoin, Citric Acid, Fragrance, FD&C Blue No.1, FD&C Yellow No.5.